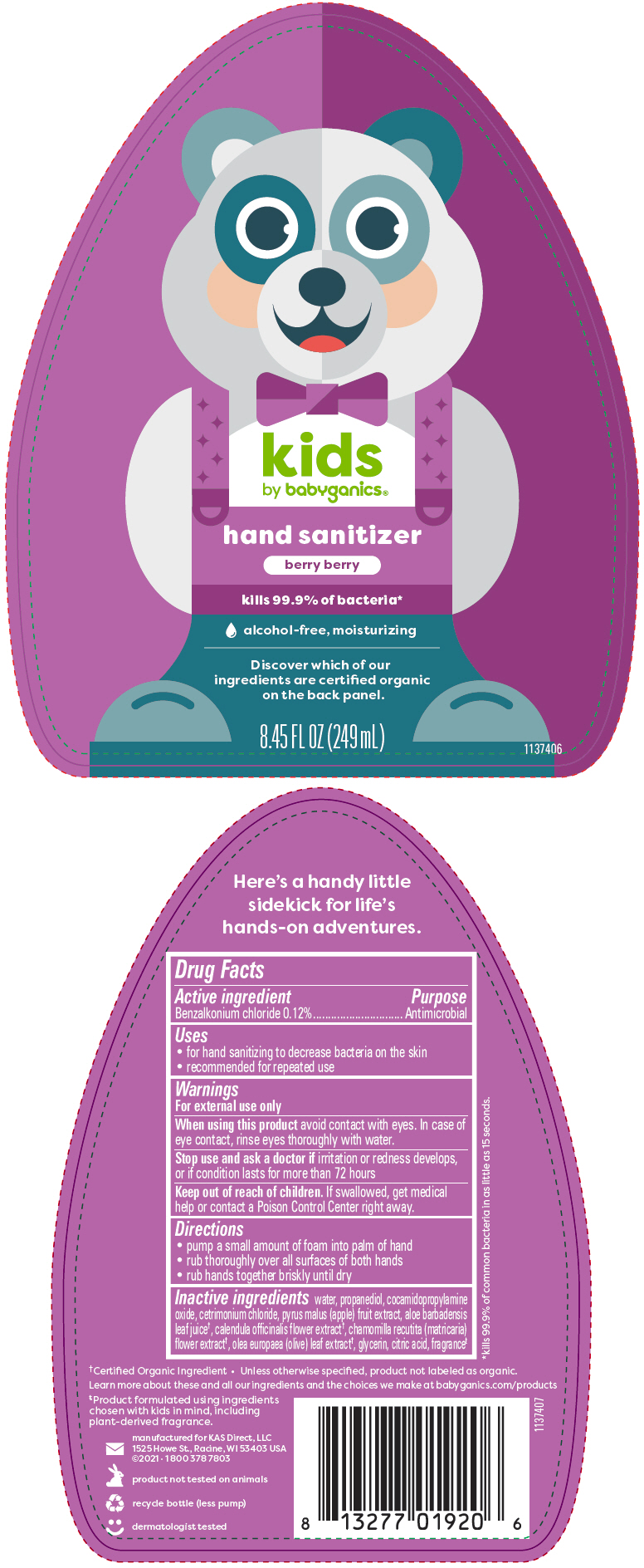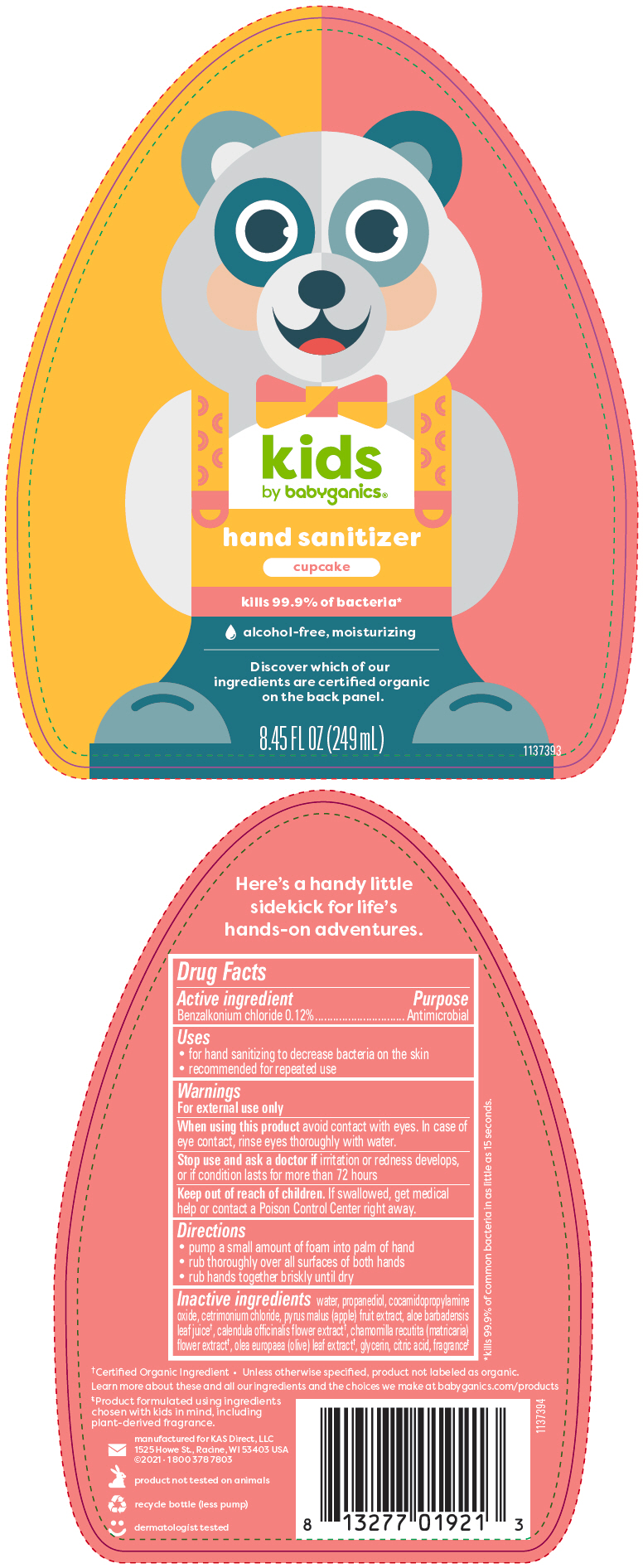 DRUG LABEL: BabyGanics Kids Alcohol Free Foaming Hand Sanitizer Berry Berry 
NDC: 59062-4101 | Form: LIQUID
Manufacturer: KAS Direct LLC dba BabyGanics
Category: otc | Type: HUMAN OTC DRUG LABEL
Date: 20251212

ACTIVE INGREDIENTS: BENZALKONIUM CHLORIDE 0.12 mg/1 mL
INACTIVE INGREDIENTS: WATER; PROPANEDIOL; COCAMIDOPROPYLAMINE OXIDE; APPLE; ALOE VERA LEAF; CALENDULA OFFICINALIS FLOWER; CHAMOMILE; OLIVE OIL; GLYCERIN; CETRIMONIUM CHLORIDE; CITRIC ACID MONOHYDRATE

BabyGanics® Kids Alcohol Free Foaming Hand Sanitizer

Drug Facts

Active ingredient

Benzalkonium chloride 0.12%

Purpose

Antimicrobial

Uses

- for hand sanitizing to decrease bacteria on the skin
- recommended for repeated use

Warnings

For external use only

When using this product avoid contact with eyes. In case of eye contact, rinse eyes thoroughly with water.

Stop use and ask a doctor if irritation or redness develops, or if condition lasts for more than 72 hours

Keep out of reach of children. If swallowed, get medical help or contact a Poison Control Center right away.

Directions

- pump a small amount of foam into palm of hand
- rub thoroughly over all surfaces of both hands
- rub hands together briskly until dry

Inactive ingredients

water, propanediol, cocamidopropylamine oxide, cetrimonium chloride, pyrus malus (apple) fruit extract, aloe barbadensis leaf juice [Certified Organic Ingredient • Unless otherwise specified, product not labeled as organic. Learn more about these and all our ingredients and the choices we make at babyganics.com/products] , calendula officinalis flower extract, chamomilla recutita (matricaria) flower extract, olea europaea (olive) leaf extract, glycerin, citric acid, fragrance [Product formulated using ingredients chosen with kids in mind, including plant-derived fragrance.]

PRINCIPAL DISPLAY PANEL - 249 mL Bottle Label - NDC 59062-4101

kids
by babyganics®

hand sanitizer
berry berry

kills 99.9% of bacteria*

alcohol-free, moisturizing

Discover which of our
ingredients are certified organic
on the back panel.

8.45 FL OZ (249 mL)

1137406

PRINCIPAL DISPLAY PANEL - 249 mL Bottle Label - NDC 59062-4201

kids
by babyganics®

hand sanitizer
cupcake

kills 99.9% of bacteria*

alcohol-free, moisturizing

Discover which of our
ingredients are certified organic
on the back panel.

8.45 FL OZ (249 mL)

1137393